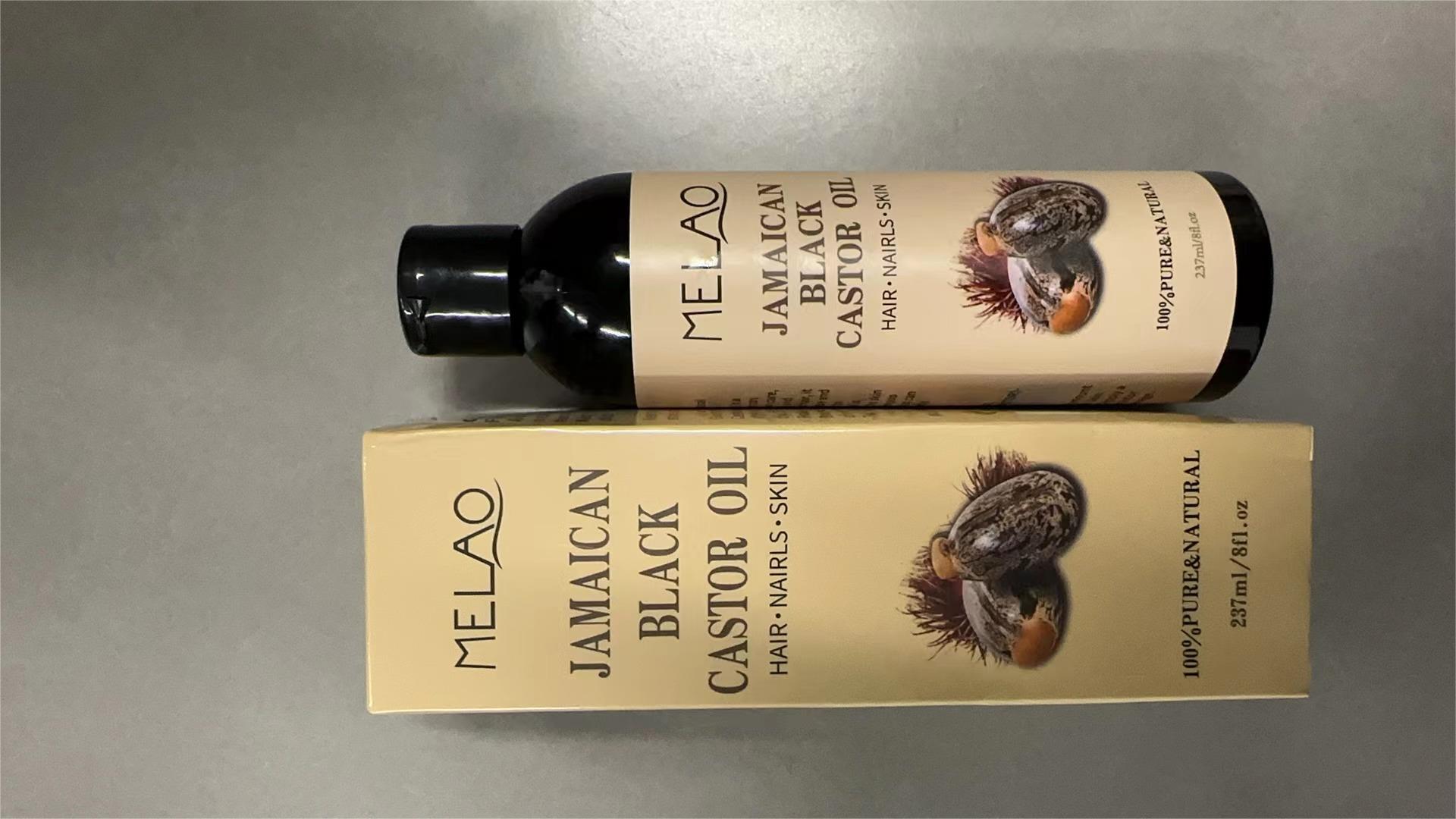 DRUG LABEL: MELAO JAMAICAN BLACK CASTOR Oil
NDC: 83566-574 | Form: LIQUID
Manufacturer: Guangzhou Yilong Cosmetics Co., Ltd
Category: otc | Type: HUMAN OTC DRUG LABEL
Date: 20240808

ACTIVE INGREDIENTS: CASTOR OIL 99 g/100 g
INACTIVE INGREDIENTS: CASTOR OIL FISH 1 g/100 g

MELAO JAMAICAN BLACK CASTOR OIL

Active ingredients

Castor Oil Benzoate 99%

Inactive ingredients

CASTOR OIL FISH 1%

Purpose

hair care

Uses

Step 1: Clean and thoroughly dry your hair.
Step 2: Squeeze out an appropriate amount of oil.
Step 3: Gently apply to the surface of the hair.

Warning

For external use only.

Stop use and ask a doctor if

rash occurs

Do not use

on damaged or broken skin.

When using this product

keep out of eyes. Rinse withwater to remove.

Keep out of reach of children.

-If swallowed, get medical help or contact a Poison Control Center right away.

DOSAGE & ADMINISTRATION

Squeeze out an appropriate amount of sunscreen and spread evenly on skin.